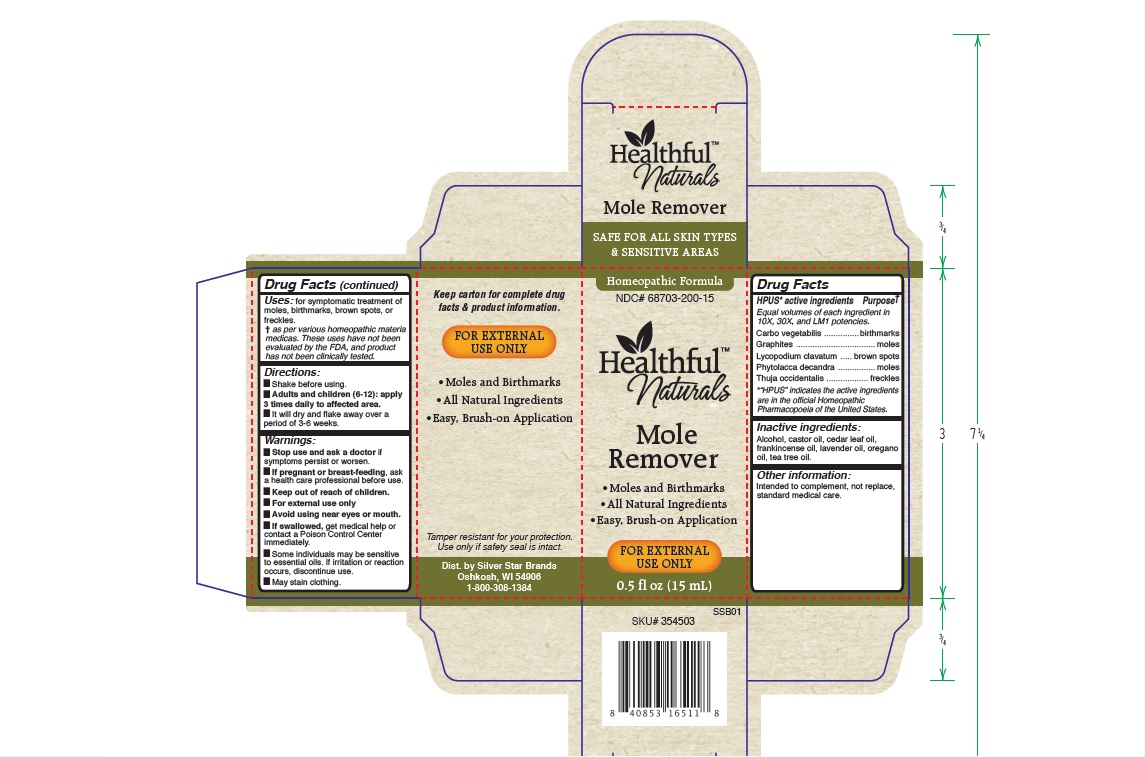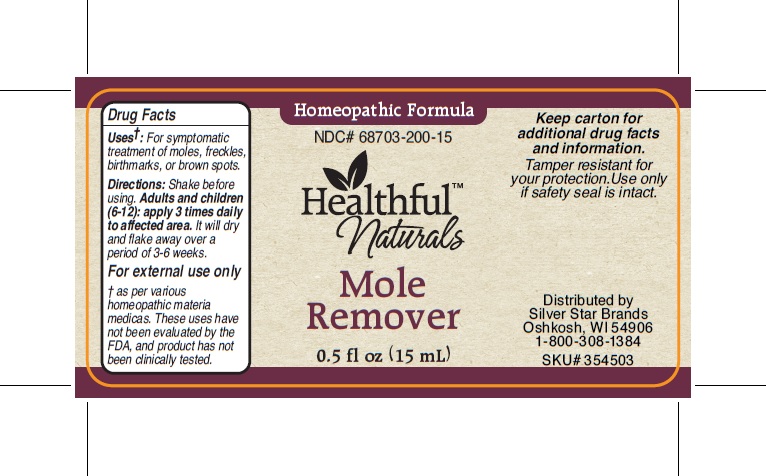 DRUG LABEL: Healthful Naturals Mole Remover
NDC: 68703-200 | Form: LIQUID
Manufacturer: Silver Star Brands
Category: homeopathic | Type: HUMAN OTC DRUG LABEL
Date: 20160108

ACTIVE INGREDIENTS: CARBO ANIMALIS 10 [hp_X]/15 mL; GRAPHITE 10 [hp_X]/15 mL; PHYTOLACCA AMERICANA ROOT 10 [hp_X]/15 mL; LYCOPODIUM CLAVATUM SPORE 10 [hp_X]/15 mL; THUJA OCCIDENTALIS LEAFY TWIG 10 [hp_X]/15 mL
INACTIVE INGREDIENTS: FRANKINCENSE OIL; ALCOHOL; CASTOR OIL; CEDAR LEAF OIL; LAVENDER OIL; OREGANO LEAF OIL; TEA TREE OIL

Healthful Naturals Mole Remover

HPUS active ingredients

Equal volumes of each ingredient in 10X, 30X, and LM1 potencies: Carbo vegetabilis, Graphites, Lycopodium clavatum, Phytolacca decandra, Thuja occidentalis.

Warnings

- Stop use and ask a doctor if symptoms persist or worsen.
- If pregnant or breast-feeding, ask a healthcare professional before use.
- Keep out of reach of children.
- For external use only.
- Avoid using near eyes or mouth.
- If swallowed, get medical help or contact a Poison Control Center immediately.
- Some individuals may be sensitive to essential oils. If irritation or reaction occurs, discontinue use.
- May stain clothing.

Uses

for symptomatic treatment of moles, birthmarks, brown spots, or freckles.

Directions

- Shake before using.
- Adults and children (6-12): apply 3 times daily to affected area.
- It will dry and flake away over a period of 3-6 weeks.

Other Information

- Intended to complement, not replace, standard medical care.
- Tamper resistant for your protection. Use only if safety seal is intact.

Drug Facts

HPUS active ingredients Purpose

Equal volumes of each ingredient in 10X, 30X, and LM1 potencies.

Carbo vegetabilis........................................................birthmarks

Graphites...................................................................moles

Lycopodium clavatum..................................................brown spots

Phytolacca decandra....................................................moles

Thuja occidentalis........................................................freckles

Keep out of reach of children.

INACTIVE INGREDIENT

Alcohol, castor oil, cedar leaf oil, frankincense oil, lavender oil, oregano oil, tea tree oil